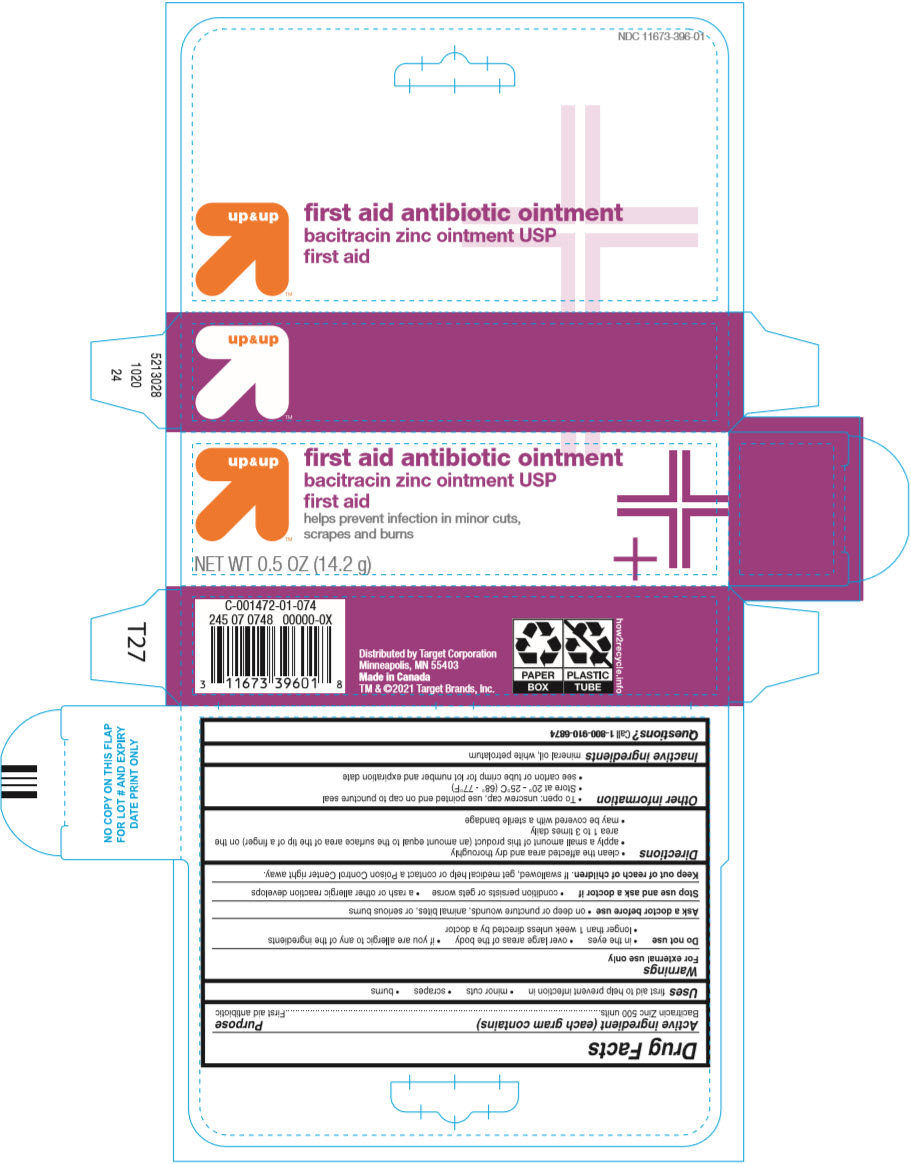 DRUG LABEL: First Aid Antibiotic
NDC: 11673-396 | Form: OINTMENT
Manufacturer: TARGET Corporation
Category: otc | Type: HUMAN OTC DRUG LABEL
Date: 20250707

ACTIVE INGREDIENTS: BACITRACIN ZINC 500 [USP'U]/1 g
INACTIVE INGREDIENTS: MINERAL OIL; PETROLATUM

First Aid Antibiotic Ointment
Bacitracin Zinc

Drug Facts

Active ingredient (each gram contains)

Bacitracin Zinc 500 units

Purpose

First aid antibiotic

Uses

first aid to help prevent infection in

- minor cuts
- scrapes
- burns

Warnings

For external use only

Do not use

- in the eyes
- over large areas of the body
- if you are allergic to any of the ingredients
- longer than 1 week unless directed by a doctor

Ask a doctor before use

- on deep or puncture wounds, animal bites, or serious burns

Stop use and ask a doctor if

- condition persists or gets worse
- a rash or other allergic reaction develops

Keep out of reach of children.If swallowed, get medical help or contact a Poison Control Center right away.

Directions

- clean the affected area and dry thoroughly
- apply a small amount of this product (an amount equal to the surface area of the tip of a finger) on the area 1 to 3 times daily
- may be covered with a sterile bandage

Other information

- To open: unscrew cap, use pointed end on cap to puncture seal
- Store at 20° - 25°C (68° - 77°F)
- see carton or tube crimp for lot number and expiration date

Inactive ingredients

mineral oil, white petrolatum

Questions?

Call 1-800-910-6874

Distributed by Target Corporation
Minneapolis, MN 55403

PRINCIPAL DISPLAY PANEL - 14.2 g Tube Carton

up & up

ﬁrst aid antibiotic ointment
bacitracin zinc ointment USP
first aid

helps prevent infection in minor cuts,
scrapes and burns

NET WT 0.5 OZ (14.2 g)